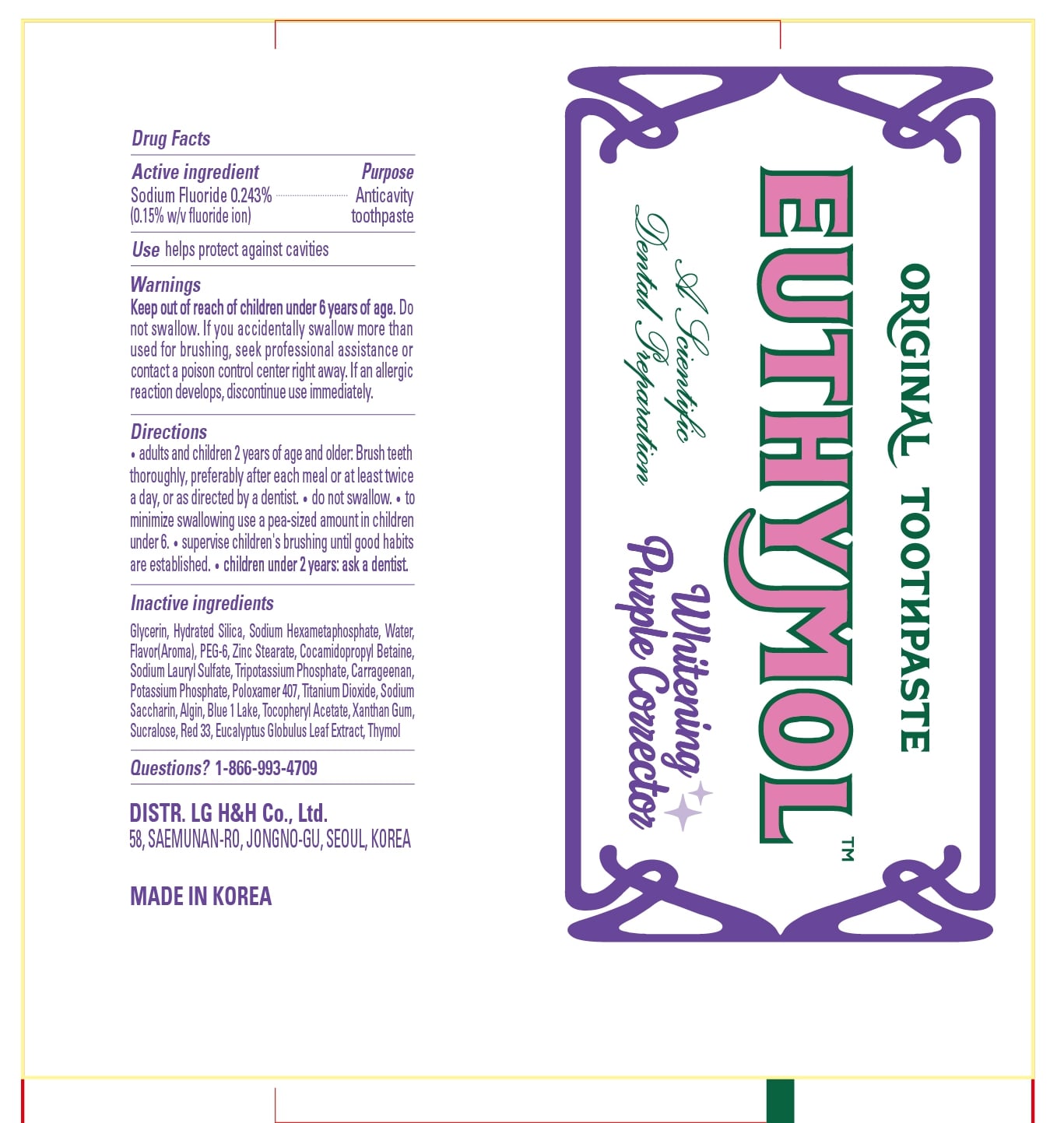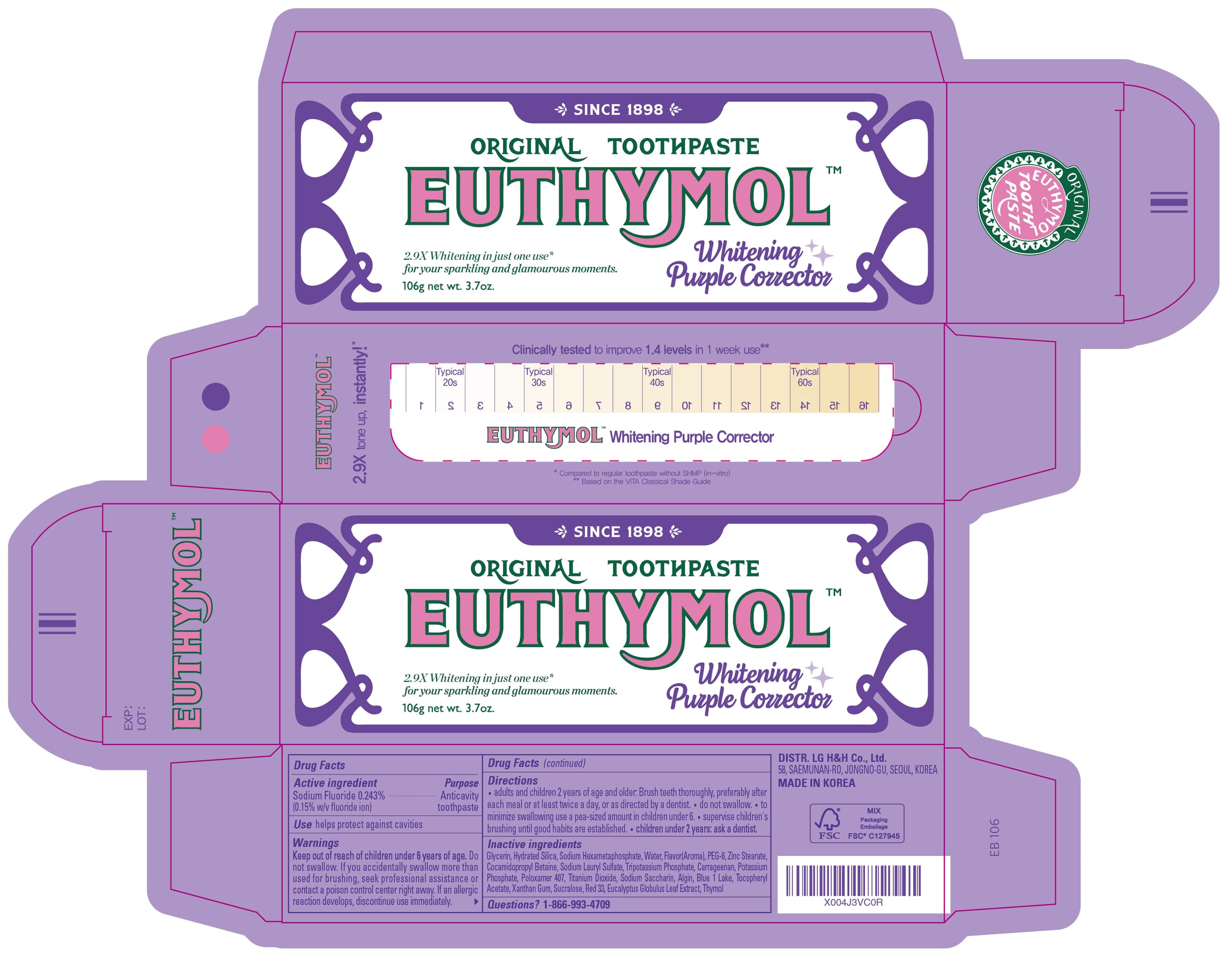 DRUG LABEL: Euthymol Whitening Purple Corrector
NDC: 53208-563 | Form: PASTE, DENTIFRICE
Manufacturer: LG HOUSEHOLD & HEALTH CARE LTD.
Category: otc | Type: HUMAN OTC DRUG LABEL
Date: 20250409

ACTIVE INGREDIENTS: SODIUM FLUORIDE 1.5 mg/1 g
INACTIVE INGREDIENTS: POTASSIUM PHOSPHATE; POLOXAMER 407; CARRAGEENAN; ALPHA-TOCOPHEROL ACETATE; XANTHAN GUM; SUCRALOSE; GLYCERIN; SODIUM HEXAMETAPHOSPHATE; THYMOL; RED 33; HYDRATED SILICA; ALGIN; BLUE 1 LAKE; COCAMIDOPROPYL BETAINE; ZINC STEARATE; TITANIUM DIOXIDE; WATER; SODIUM SACCHARIN; EUCALYPTUS GLOBULUS LEAF; PEG-6; SODIUM LAURYL SULFATE; POTASSIUM PHOSPHATE, TRIBASIC

Active ingredient

Sodium Fluoride 0.243%

(0.15% w/v fluoride ion)

Purpose

Anticavity toothpaste

Use

helps protect against cavities

WARNINGS

Keep out of reach of children under 6 years of age.

Do not

Do not swallow. If you accidentally swallow more than used for brushing, seek professional assistance or contact a poison control center right away. If an allergic reaction develops, discontinue use immediately.

Directions

- adults and children 2 years of age and older. Brush teeth thoroughly, preferably after each meal or at least twice a day, or as directed by a dentist.
- do not swallow.
- to minimize swallowing use a pea-sized amount in children under 6.
- supervise children's brushing until good habits are established.
- children under 2 years: ask a dentist.

Inactive ingredients

GLYCERIN, HYDRATED SILICA, SODIUM HEXAMETAPHOSPHATE, WATER, FLAVOR(AROMA), PEG-6, ZINC STEARATE, COCAMIDOPROPYL BETAINE, SODIUM LAURYL SULFATE, TRIPOTASSIUM PHOSPHATE, CARRAGEENAN, POTASSIUM PHOSPHATE, POLOXAMER 407, TITANIUM DIOXIDE, SODIUM SACCHARIN, ALGIN, BLUE 1 LAKE, TOCOPHERYL ACETATE, XANTHAN GUM, SUCRALOSE, RED 33, EUCALYPTUS GLOBULUS LEAF EXTRACT, THYMOL

Questions?

1-866-993-4709